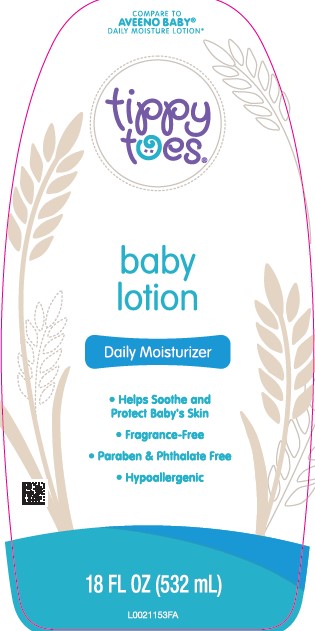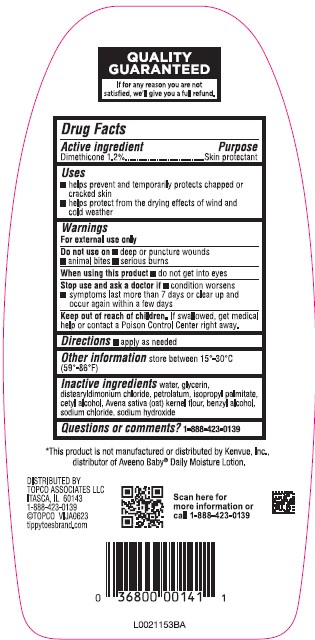 DRUG LABEL: Dimethicone
NDC: 76162-496 | Form: LOTION
Manufacturer: Topco Associates LLC
Category: otc | Type: HUMAN OTC DRUG LABEL
Date: 20260213

ACTIVE INGREDIENTS: DIMETHICONE 12 mg/1 mL
INACTIVE INGREDIENTS: GLYCERIN; DISTEARYLDIMONIUM CHLORIDE; PETROLATUM; ISOPROPYL PALMITATE; CETYL ALCOHOL; OATMEAL; BENZYL ALCOHOL; SODIUM CHLORIDE; SODIUM HYDROXIDE; WATER

Tippy Toes 496.000/496AA
Daily Baby Lotion with Colloidal Oatmeal

QUALITY GUARANTEED

If for any reason you are not satisfied, we'll give you a full refund.

Active ingredient

Dimethicone 1.2%

Purpose

Skin protectant

Uses

- helps prevent and temporarily protects chapped or cracked skin
- helps protect from the drying effects of wind and cold weather

Warnings

For external use only

Do not use on

- deep or punture wounds
- animal bites
- serious burns

When using this product

- do not get into eyes

Stop use and ask a doctor if

- condition worsens
- symptoms last more then 7 days or clear up and occur again within a few days

Keep out of reach of children.

If swallowed, get medical help or contact a Poison Control Center right away.

Directions

- apply as needed

Other information

store between 15°-30°C (59°-86°F)

Inactive ingredients

water, glycerin, distearyldimonium chloride, petrolatum, isopropyl palmitate, cetyl alcohol, Avena sativa (oat) kernel flour, benzyl alcohol, sodium chloride, sodium hydroxide

Questions or comments?

1-888-423-0139

Disclaimer

*This product is not manufactured or distributed by Kenvue, Inc., distributor of Aveeno Baby® Daily Moisture Lotion.

Adverse reaction

DISTRIBUTED BY

TOPCO ASSOCIATES LLC

ITASCA, IL 60143

1-888-423-0139

©TOPCO VIJA0623

tippytoesbrand.com

Scan here for more information or call 1-888-423-0139

Principal panel display

COMPARE TO AVEENO BABY® DAILY MOISTURE LOTION*

tippy toes®

baby lotion

Daily Moisturizer

- Helps Soothe and Protect Baby's Skin
- Fragrance-Free
- Paraben & Phthalate Free
- Hypoallergenic

18 FL OZ (532 mL)